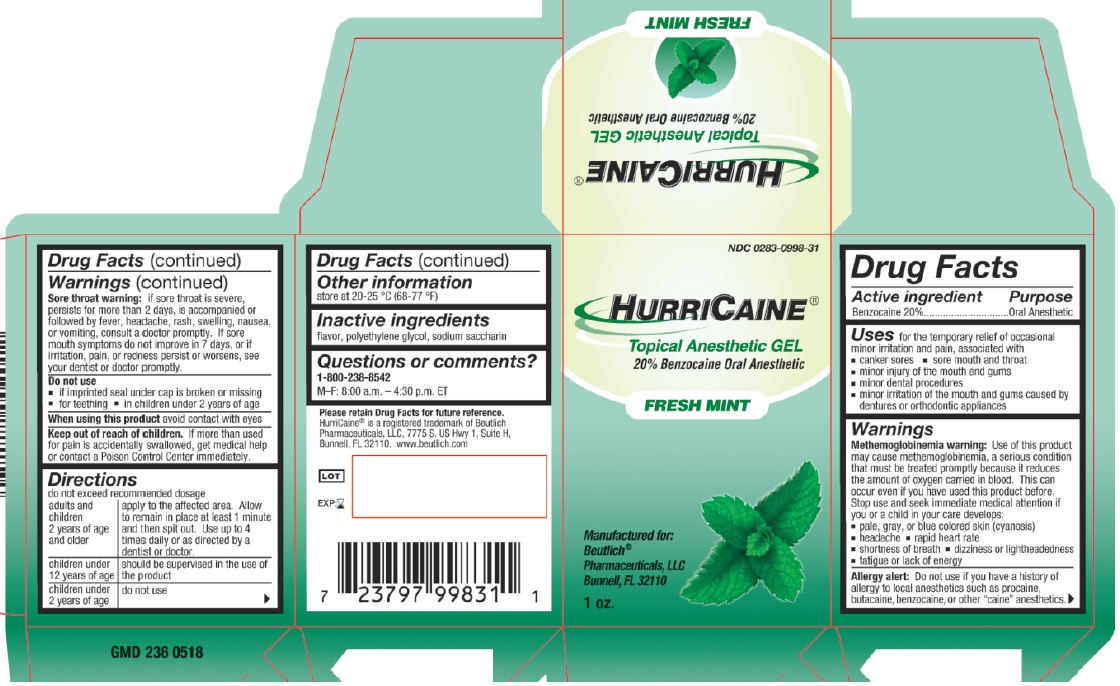 DRUG LABEL: HurriCaine
NDC: 0283-0998 | Form: GEL
Manufacturer: Beutlich Pharmaceuticals LLC
Category: otc | Type: HUMAN OTC DRUG LABEL
Date: 20250108

ACTIVE INGREDIENTS: BENZOCAINE 200 mg/1 g
INACTIVE INGREDIENTS: POLYETHYLENE GLYCOL 400; POLYETHYLENE GLYCOL 3350; SACCHARIN SODIUM

Mint Gel 1oz

Active ingedient

Benzocaine 20%

Purpose

Oral Anesthetic

Uses

for the temporary relief of occasional minor irritation and pain, associated with:

- canker sores
- sore mouth and throat
- minor injury of the mouth and gums
- minor dental procedures
- minor irritation of the mouth and gums caused by dentures or orthodontic appliances

Warnings

Allergy alert: Do not use if you have a history of allergy to local anesthetics such as procaine, butaine, benzocaine or other "caine" anesthetics.

Stop use and ask doctor if

- sore throat is severe, persists for more than 2 days, is accompanied or followed by a fever, headache, rash, swelling, nausea or vomiting
- sore mouth symptoms do not improve in 7 days, or if irritation, pain, or redness persists or worsens

When using this product

- avoid contact with eyes

Keep out of reach of children.

If more than used for pain is accidentally swallowed, get medical help or contact a Poison Control Center immediately.

Adverse Reactions:

Methemoglobinemia has been reported following the use of benzocaine on extremely rare occasions. Intravenous methylene blue is the specific therapy for this condition.

Directions

- do not exceed recommend dosage

adults and children 2 years of age and older: apply to the affected area. Allow to remain in place at least 1 minute and then spit out. Use up to 4 times daily or as directed by a dentist or doctor.

children under 12 years of age: should be supervised in the use of the product

children under 2 years of age: consult a dentist or doctor

Other information

- do not use if imprinted seal under cap is broken or missing
- store at 20-25 °C (68-77 °F)

Inactive ingredient

flavor, polyethylene glycol, sodium saccharin

Questions or comments?

1-800-238-8542

M-F: 8:00 a.m. - 4:30 p.m. ET

Principal Display Panel

NDC 0283-0998-31

HURRICAINE®

Topical Anesthetic GEL

20% Benzocaine Oral Anesthetic

FRESH MINT

Manufactured for:

Beutlich®

Pharmaceuticals, LLC

Bunnell, FL

www.beutlich.com